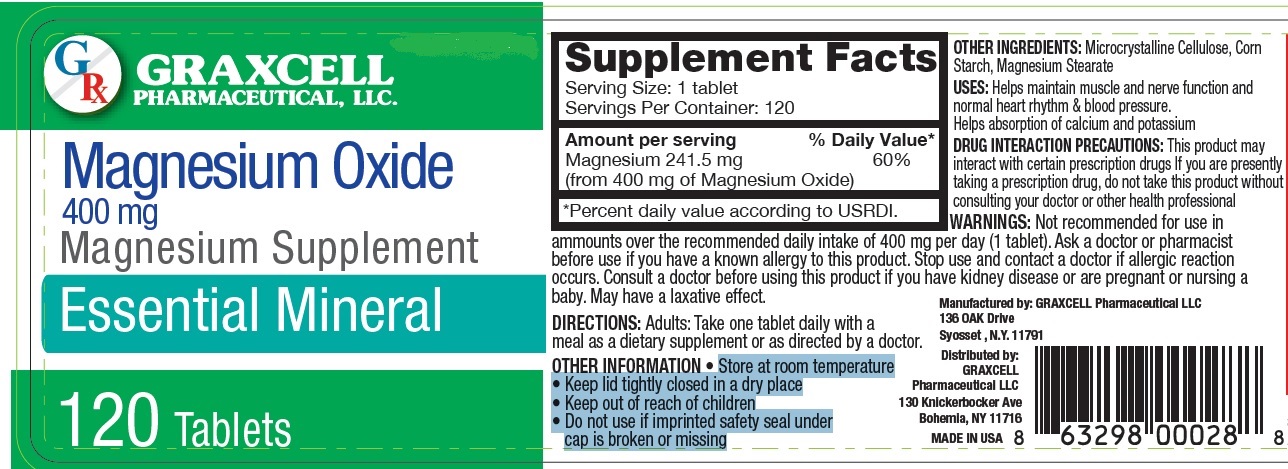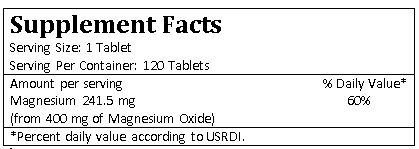 DRUG LABEL: Magnesium Oxide
NDC: 70795-1152 | Form: TABLET
Manufacturer: GRAXCELL PHARMACEUTICAL, LLC
Category: other | Type: DIETARY SUPPLEMENT
Date: 20211221

ACTIVE INGREDIENTS: Magnesium Oxide 400 mg/1 1
INACTIVE INGREDIENTS: MICROCRYSTALLINE CELLULOSE; STARCH, CORN; MAGNESIUM STEARATE

GRAXCELL PHARMACEUTICAL MAGNESIUM OXIDE 400 MG, 70795-1152

USES

- Helps maintain muscle and nerve function and normal heart rhythm & blood pressure.
- Helps absorption of calcium and potassium

DRUG INTERACTION PRECAUTIONS:

This product may interact with certain prescription drugs If you are presently taking a prescription drug, do not take this product without

consulting your doctor or other health professional

WARNINGS

Not recommended for use in ammounts over the recommended daily intake of 400 mg per day (1 tablet). Ask a doctor or pharmacist

before use if you have a known allergy to this product. Stop use and contact a doctor if allergic reaction occurs. Consult a doctor before using this product if you have kidney disease or are pregnant or nursing a baby. May have a laxative effect.

DIRECTIONS

Adults: Take one tablet daily with a meal as a dietary supplement or as directed by a doctor

OTHER INGREDIENTS

Microcrystalline Cellulose, Corn Starch, Magnesium Stearate

OTHER INFORMATION

- Store at room temperature
- Keep lid tightly closed in a dry place
- Keep out of reach of children
- Do not use if imprinted safety seal under cap is broken or missing